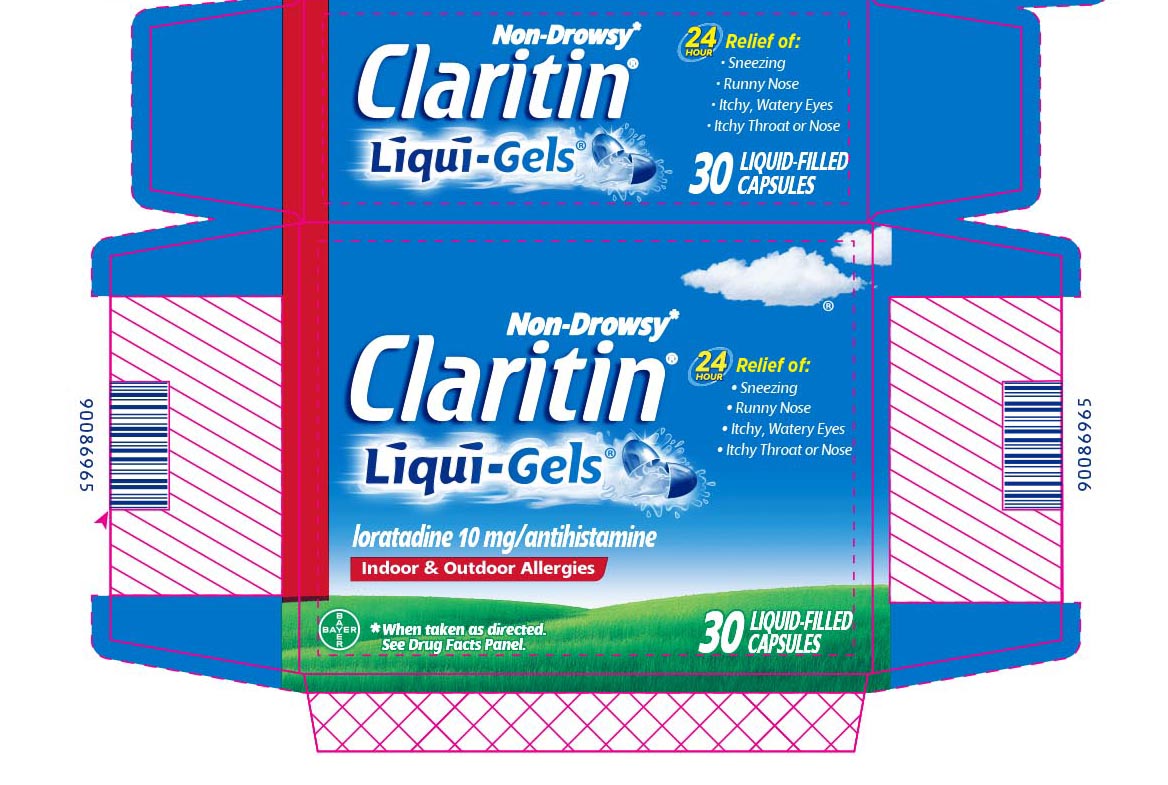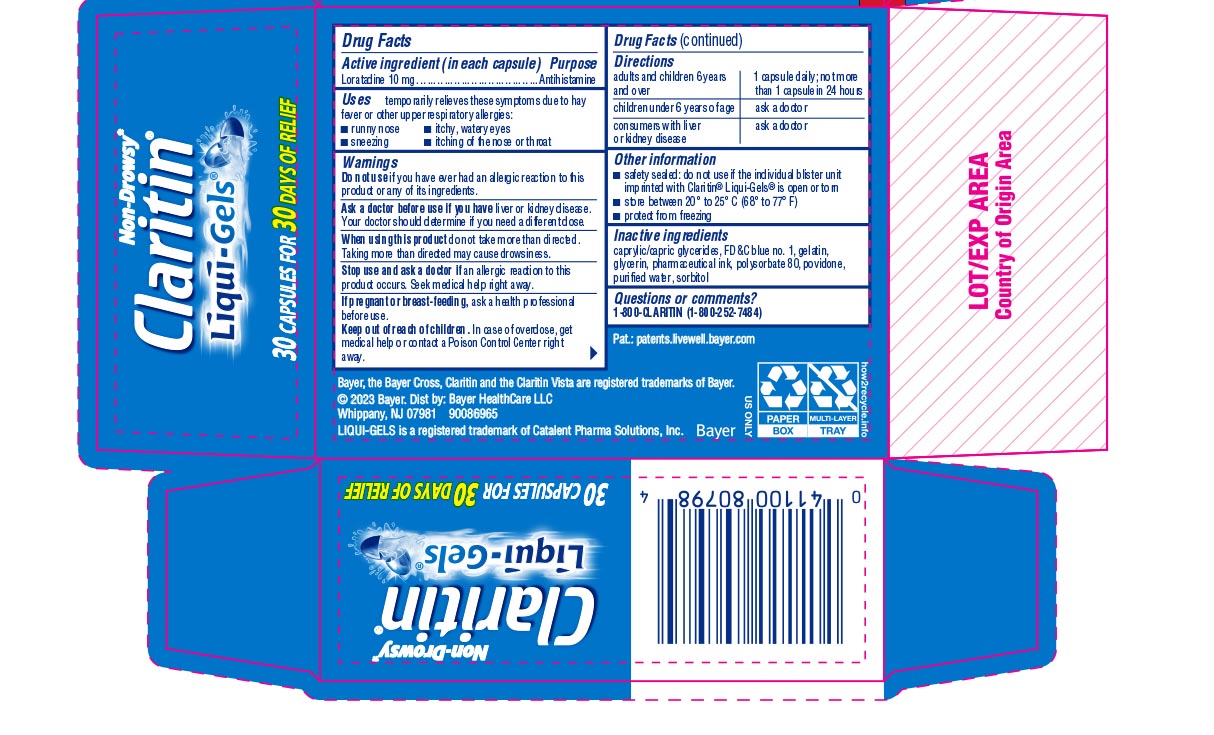 DRUG LABEL: Claritin
NDC: 11523-7200 | Form: CAPSULE, LIQUID FILLED
Manufacturer: Bayer HealthCare LLC.
Category: otc | Type: HUMAN OTC DRUG LABEL
Date: 20260206

ACTIVE INGREDIENTS: LORATADINE 10 mg/1 1
INACTIVE INGREDIENTS: GELATIN; GLYCERIN; POLYSORBATE 80; POVIDONE; WATER; SORBITOL; FD&C BLUE NO. 1

Claritin®
Liqui-Gels®

Drug Facts

Active ingredient (in each capsule)

Loratadine 10 mg

Purpose

Antihistamine

Uses

temporarily relieves these symptoms due to hay fever or other upper respiratory allergies:

- runny nose
- itchy, watery eyes
- sneezing
- itching of the nose or throat

Warnings

Do not use if you have ever had an allergic reaction to this product or any of its ingredients.

Ask a doctor before use if you have liver or kidney disease. Your doctor should determine if you need a different dose.

When using this product do not take more than directed. Taking more than directed may cause drowsiness.

Stop use and ask a doctor if an allergic reaction to this product occurs. Seek medical help right away.

PREGNANCY OR BREAST FEEDING

If pregnant or breast-feeding, ask a health professional before use.

Keep out of reach of children. In case of overdose, get medical help or contact a Poison Control Center right away.

Directions

adults and children 6 years and over | 1 capsule daily; not more than 1 capsule in 24 hours
children under 6 years of age | ask a doctor
consumers with liver or kidney disease | ask a doctor

Other information

- safety sealed: do not use if the individual blister unit imprinted with Claritin® Liqui-Gels® is open or torn
- store between 20° to 25°C (68° to 77°F)
- protect from freezing

Inactive ingredients

caprylic/capric glycerides, FD&C blue no.1, gelatin, glycerin, pharmaceutical ink, polysorbate 80, povidone, purified water, sorbitol

Questions or comments?

1-800-CLARITIN (1-800-252-7484)

Pat.: patents.livewell.bayer.com

Bayer, the Bayer Cross, Claritin and the Claritin Vista are registered trademarks of Bayer.

© 2023 Bayer. Dist by: Bayer HealthCare LLC

Whippany, NJ 07981

LIQUI-GELS is a registered trademark of Catalent Pharma Colutions, Inc.

PRINCIPAL DISPLAY PANEL - 30 Capsule Carton

Non-Drowsy*
Claritin ®
Liqui-Gels®

24
Hour

Relief of:

- Sneezing
- Runny Nose
- Itchy, Watery Eyes
- Itchy Throat or Nose

loratadine 10 mg/antihistamine

Indoor & Outdoor Allergies
Allergies

*When taken as directed.
See Drug Facts Panel.

30 LIQUID-FILLED
CAPSULES